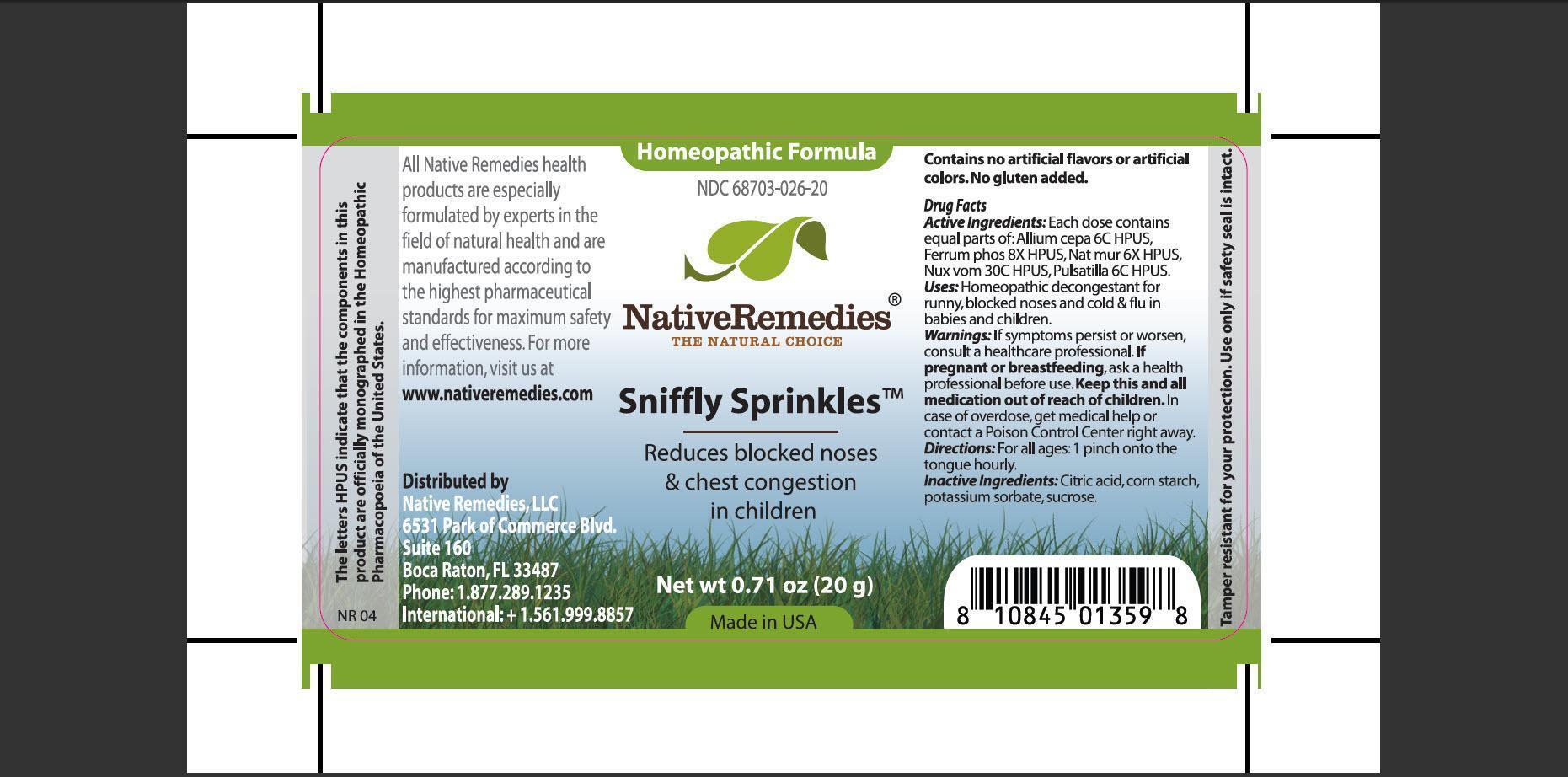 DRUG LABEL: Sniffly Sprinkles
                
NDC: 68703-026 | Form: GRANULE
Manufacturer: Native Remedies, LLC
Category: homeopathic | Type: HUMAN OTC DRUG LABEL
Date: 20130130

ACTIVE INGREDIENTS: ONION 6 [hp_C]/16 mg; FERROSOFERRIC PHOSPHATE 8 [hp_X]/16 mg; SODIUM CHLORIDE 6 [hp_X]/16 mg; STRYCHNOS NUX-VOMICA SEED 30 [hp_C]/16 mg; PULSATILLA VULGARIS 6 [hp_C]/16 mg
INACTIVE INGREDIENTS: CITRIC ACID MONOHYDRATE; STARCH, CORN; POTASSIUM SORBATE; SUCROSE

Sniffly Sprinkles

PURPOSE

Reduces blocked noses and chest congestion in children

ACTIVE INGREDIENT

Active Ingredients: Each dose contains equal parts of: Allium cepa 6C HPUS, Ferrum phos 8X HPUS, Nat mur 6X HPUS, Nux vom 30C HPUS, Pulsatilla 6C HPUS.

INDICATIONS AND USAGE

Uses:Homeopathic decongestant for runny, blocked noses and cold and flu in babies and children.

WARNINGS

Warnings: If symptoms persist or worsen, consult a healthcare professional.

PREGNANCY OR BREAST FEEDING

If pregnant or breastfeeding, ask a health professional before use.

KEEP OUT OF REACH OF CHILDREN

Keep this and all medication out of reach of children.

OVERDOSAGE

In case of overdose, get medical help or contact a Poison Control Center right away.

DOSAGE AND ADMINISTRATION

Directions: For all ages: 1 pinch onto the tongue hourly.

INACTIVE INGREDIENT

Inactive Ingredients: Citric acid, corn starch, potassium sorbate, sucrose.

PATIENT COUNSELING INFORMATION

The letters HPUS indicate that the components in this product are officially monographed in the Homeopathic Pharmacopoeia of the United States.

All Native Remedies health products are especially formulates by experts in the field of natural health and are manufactures according to the highest pharmaceutical standards for maximum safety and effectiveness. For more information, visit us at www.nativeremedies.com

Distributed by
Native Remedies, LLC
6531 Park of Commerce Blvd.
Suite 160
Boca Raton, Fl 33487
Phone: 1.877.289.1235
International:+1.561.999.8857

Contains no artificial flavors or artificial colors. No gluten added.

STORAGE AND HANDLING

Tamper resistant for your protection. Use only if safety seal is intact.